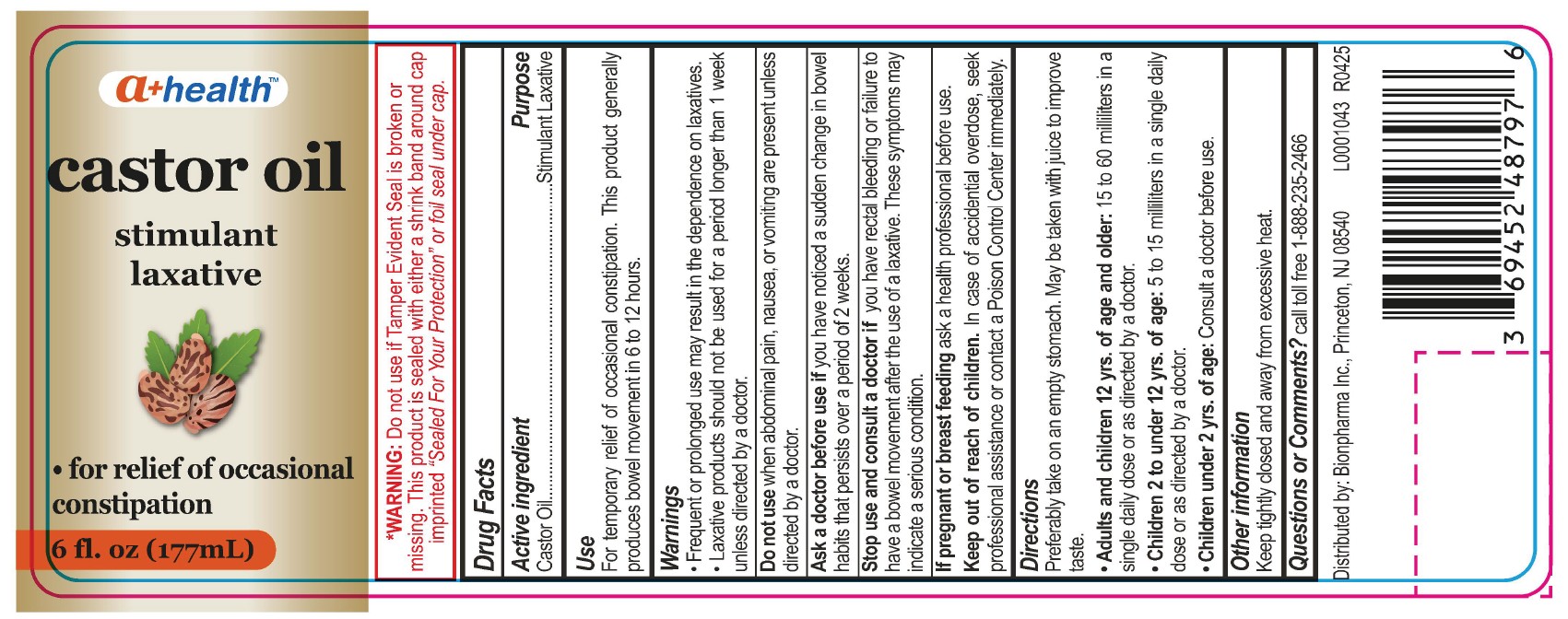 DRUG LABEL: Castor Oil
NDC: 69452-487 | Form: LIQUID
Manufacturer: BIONPHARMA INC.
Category: otc | Type: HUMAN OTC DRUG LABEL
Date: 20251006

ACTIVE INGREDIENTS: CASTOR OIL 1 mg/1 mL
INACTIVE INGREDIENTS: WATER

a+ Health-castor oil

Drug Facts

Active Ingredient

Castor Oil

Purpose

Stimulant Laxative

Use

For temporary relief of occasional constipation. This product generally produces bowel movement in 6 to 12 hours.

Warings

• Frequent or prolonged use may result in the dependence on laxatives.
• Laxative products should not be used for a period longer than 1 week unless directed by a doctor.

Do not use when abdominal pain, nausea, or vomiting are present unless directed by a doctor.

Ask a doctor before use if you have noticed a sudden change in bowel habits that persists over a period of 2 weeks.

Stop use and consult a doctor if you have rectal bleeding or failure to have a bowel movement after the use of a laxative. These symptoms may indicate a serious condition.

PREGNANCY OR BREAST FEEDING

If pregnant or breast feeding ask a health professional before use.

Keep out of reach of children. In case of accidential overdose, seek professional assistance or contact a Poison Control Center immediately.

Directions

Preferably take on an empty stomach. May be taken with juice to improve taste.

- Adults and children 12 yrs. of age and older: 15 to 60 milliliters in a single daily dose or as directed by a doctor.
- Children 2 to under 12 yrs. of age: 5 to 15 milliliters in a single daily dose or as directed by a doctor.
- Children under 2 yrs. of age: Consult a doctor before use.

Other Information

Keep tightly closed and away from excessive heat.

INACTIVE INGREDIENT

None.

Questions or Comments?

call toll free 1-888-235-2466

*WARNING: Do not use if Tamper Evident Seal is broken or missing. This product is sealed with either a shrink band around cap imprinted “Sealed For Your Protection” or foil seal under cap.

Distributed by: Bionpharma Inc., Princeton, NJ 08540 L0001043 R0425

6 fl. oz. bottle label

a+ healthTM

castor oil
stimulant
laxative
• for relief of occasional
constipation
6 fl. oz (177mL)